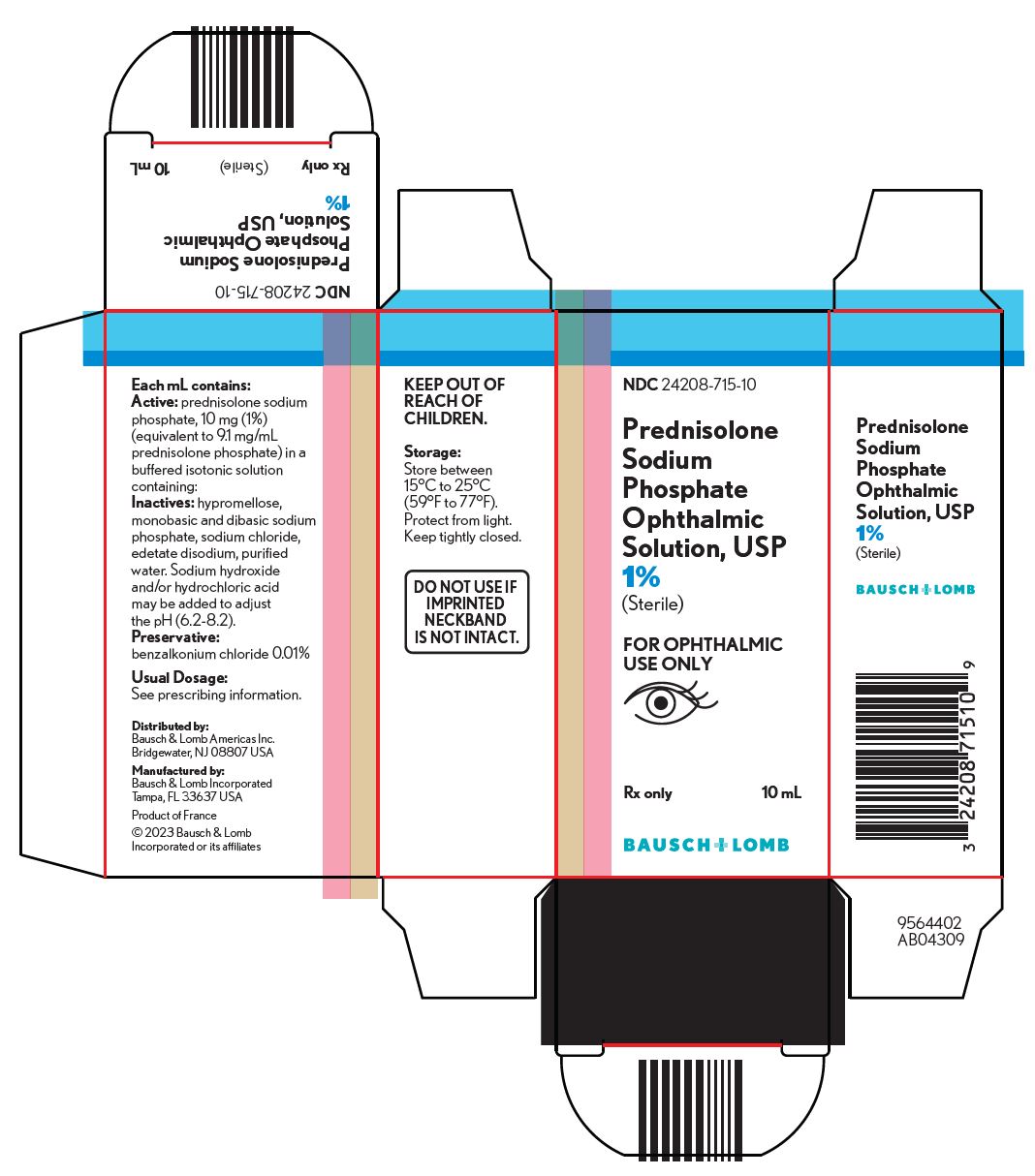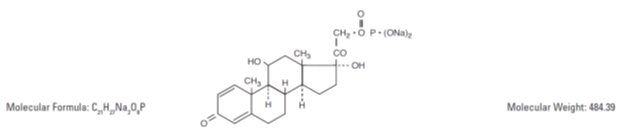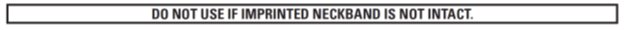 DRUG LABEL: PREDNISOLONE SODIUM PHOSPHATE
NDC: 24208-715 | Form: SOLUTION/ DROPS
Manufacturer: Bausch & Lomb Incorporated
Category: prescription | Type: HUMAN PRESCRIPTION DRUG LABEL
Date: 20230417

ACTIVE INGREDIENTS: PREDNISOLONE SODIUM PHOSPHATE 10 mg/1 mL
INACTIVE INGREDIENTS: BENZALKONIUM CHLORIDE; SODIUM PHOSPHATE, DIBASIC, UNSPECIFIED FORM; EDETATE DISODIUM; HYDROCHLORIC ACID; HYPROMELLOSE, UNSPECIFIED; SODIUM PHOSPHATE, MONOBASIC, UNSPECIFIED FORM; WATER; SODIUM CHLORIDE; SODIUM HYDROXIDE

Prednisolone Sodium
Phosphate Ophthalmic
Solution, USP
1%
(Sterile)
Rx only

DESCRIPTION

Prednisolone sodium phosphate ophthalmic solution USP, 1%, is a sterile solution for ophthalmic administration having the following composition:

Each mL contains:

Active: prednisolone sodium phosphate 10 mg (1%) [equivalent to 9.1 mg/mL prednisolone phosphate] in a buffered isotonic solution containing: Inactives: hypromellose, monobasic and dibasic sodium phosphate, sodium chloride, edetate disodium and purified water. Sodium hydroxide and/or hydrochloric acid may be added to adjust the pH (6.2-8.2).

Preservative: benzalkonium chloride 0.01%.

The chemical name for prednisolone sodium phosphate is Pregna-1, 4-diene - 3, 20-dione, 11, 17-dihydroxy-21-(phosphonooxy)-, disodium salt, (11 β) -, which has the following structural formula:

CLINICAL PHARMACOLOGY

Prednisolone sodium phosphate causes inhibition of inflammatory response to inciting agents of mechanical, chemical, or immunological nature. No generally accepted explanation of this steroid property has been advanced.

INDICATIONS AND USAGE

Prednisolone sodium phosphate ophthalmic solution, 1% or 1/8% is for the treatment of steroid responsive inflammatory conditions of the palpebral and bulbar conjunctiva, cornea, and anterior segment of the globe, such as allergic conjunctivitis, acne rosacea, superficial punctate keratitis, herpes zoster keratitis, iritis, cyclitis, selected infective conjunctivitis when the inherent hazard of steroid use is accepted to obtain an advisable diminution in edema and inflammation, corneal injury from chemical, radiation, or thermal burns, or penetration of foreign bodies.

Prednisolone sodium phosphate ophthalmic solution, 1%, is recommended for moderate to severe inflammations, particularly when unusually rapid control is desired. In stubborn cases of anterior segment eye disease, systemic adrenocortical hormone therapy may be required. When deeper ocular structures are involved, systemic therapy is necessary.

CONTRAINDICATIONS

The use of this preparation is contraindicated in the presence of:

1. Acute superficial herpes simplex keratitis.
2. Fungal diseases of ocular structures.
3. Acute infectious stages of vaccinia, varicella and most other viral diseases of the cornea and conjunctiva.
4. Tuberculosis of the eye.
5. Hypersensitivity to a component of this medication.

The use of this preparation is always contraindicated after uncomplicated removal of a superficial corneal foreign body.

WARNINGS

NOT FOR INJECTION INTO EYE - FOR TOPICAL USE ONLY

Employment of steroid medication in the treatment of herpes simplex keratitis involving the stroma requires great caution; frequent slit-lamp microscopy is mandatory.

Prolonged use may result in elevated intraocular pressure and/or glaucoma, damage to the optic nerve, defects in visual acuity and fields of vision, posterior subcapsular cataract formation, or may aid in the establishment of secondary ocular infections from pathogens liberated from ocular tissues. In those diseases causing thinning of the cornea or sclera, perforation has been known to occur with the use of topical steroids. Acute purulent untreated infection of the eye may be masked or activity enhanced by presence of steroid medication. Viral, bacterial, and fungal infections of the cornea may be exacerbated by the application of steroids.

This drug is not effective in mustard gas keratitis and Sjögren’s keratoconjuncitivitis.

If irritation persists or develops, the patient should be advised to discontinue use and consult prescribing physician.

PRECAUTIONS

General

As fungal infections of the cornea are particularly prone to develop coincidentally with long-term steroid applications, fungus invasion must be suspected in any persistent corneal ulceration where a steroid has been used or is in use.

Intraocular pressure should be checked frequently.

Information for Patients

Do not touch dropper tip to any surface as this may contaminate the solution.

Usage in Pregnancy

Animal reproductive studies have not been conducted with prednisolone sodium phosphate. It is also not known whether prednisolone sodium phosphate can cause fetal harm when administered to a pregnant woman or can affect reproductive capacity. Prednisolone sodium phosphate should be given to a pregnant woman only if clearly needed.

The effect of prednisolone sodium phosphate on the later growth, development and functional maturation of the child is unknown.

Nursing Mothers

It is not known whether this drug is excreted in human milk. Because many drugs are excreted in human milk, caution should be exercised when prednisolone sodium phosphate is administered to a nursing woman.

Pediatric Use

Safety and effectiveness in pediatric patients have not been established.

ADVERSE REACTIONS

Glaucoma with optic nerve damage, visual acuity and field defects, posterior subcapsular cataract formation, secondary ocular infections from pathogens including herpes simplex and fungi, and perforation of the globe.

Rarely, filtering blebs have been reported when topical steroids have been used following cataract surgery.

Rarely, stinging, or burning may occur.

To report SUSPECTED ADVERSE REACTIONS, contact Bausch & Lomb Incorporated at 1-800-553-5340 or FDA at 1-800-FDA-1088 or www.fda.gov/medwatch.

DOSAGE AND ADMINISTRATION

Depending on the severity of inflammation, instill one or two drops of solution into the conjunctival sac up to every hour during the day and every two hours during the night as necessary as initial therapy.

When a favorable response is observed, reduce dosage to one drop every four hours.

Later, further reduction in dosage to one drop three to four times daily may suffice to control symptoms.

The duration of treatment will vary with the type of lesion and may extend from a few days to several weeks, according to therapeutic response. Relapses, more common in chronic active lesions than in self-limited conditions, usually respond to retreatment.

HOW SUPPLIED

Prednisolone sodium phosphate ophthalmic solution USP, 1% is supplied in a plastic squeeze bottle with a white cap and a controlled drop tip in the following size:

10 mL bottle - NDC 24208-715-10

Storage: Store between 15°C to 25°C (59°F to 77°F).

Protect from light. Keep tightly closed.

Keep out of reach of children.

Distributed by:

Bausch & Lomb Americas Inc.

Bridgewater, NJ 08807 USA

Manufactured by:

Bausch & Lomb Incorporated

Tampa, FL 33637 USA

© 2023 Bausch & Lomb Incorporated or its affiliates

Revised: April 2023

9101406 (Folded)

9101506 (Flat)

PACKAGE/LABEL PRINCIPAL DISPLAY PANEL

NDC 24208-715-10

Prednisolone

Sodium

Phosphate

Ophthalmic

Solution, USP

1%

(Sterile)

FOR OPHTHALMIC USE ONLY

Rx only 10 mL

BAUSCH + LOMB

9564402